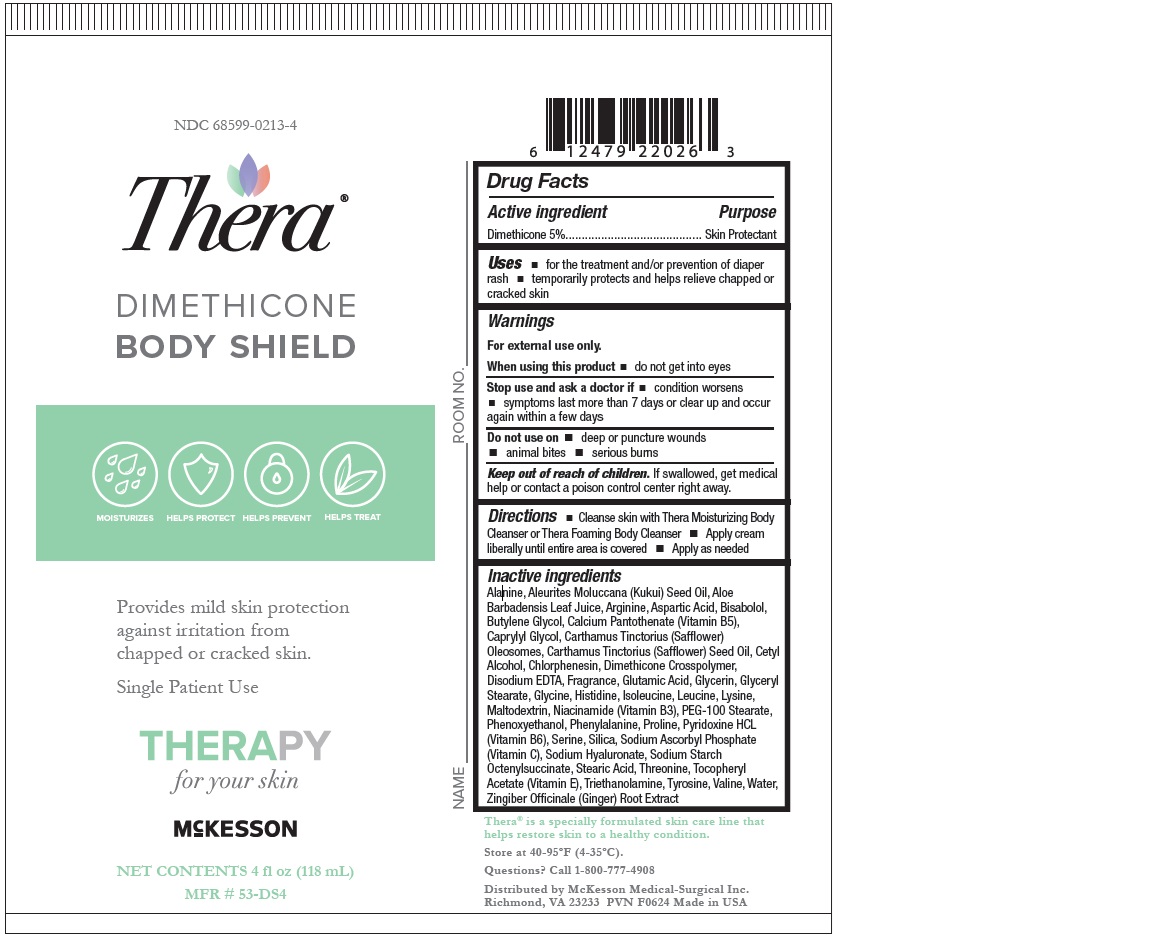 DRUG LABEL: Dimethicone
NDC: 68599-0213 | Form: CREAM
Manufacturer: McKesson
Category: otc | Type: HUMAN OTC DRUG LABEL
Date: 20241018

ACTIVE INGREDIENTS: DIMETHICONE 50 ug/1 mg
INACTIVE INGREDIENTS: CALCIUM PANTOTHENATE; SILICON DIOXIDE; CETYL ALCOHOL; SODIUM ASCORBYL PHOSPHATE; OCTENYLSUCCINIC ACID; ALOE VERA LEAF; CARTHAMUS TINCTORIUS (SAFFLOWER) OLEOSOMES; CAPRYLYL GLYCOL; PROLINE; GLYCINE; ARGININE; ASPARTIC ACID; ALANINE; LEUCINE; TYROSINE; TROLAMINE; GLYCERIN; WATER; MALTODEXTRIN; PYRIDOXINE HYDROCHLORIDE; HYALURONATE SODIUM; GINGER; LYSINE; THREONINE; GLUTAMIC ACID; ISOLEUCINE; PEG-100 STEARATE; STEARIC ACID; BUTYLENE GLYCOL; NIACINAMIDE; .ALPHA.-TOCOPHEROL ACETATE; EDETATE DISODIUM ANHYDROUS; CHLORPHENESIN; HISTIDINE; SERINE; PHENOXYETHANOL; LEVOMENOL; VALINE; PHENYLALANINE; GLYCERYL MONOSTEARATE; KUKUI NUT OIL; SAFFLOWER OIL; DIMETHICONE CROSSPOLYMER (450000 MPA.S AT 12% IN CYCLOPENTASILOXANE)

Body Shield Dimethicone

Drug Facts

Active Ingredient
Dimethicone 5%

Purpose
Skin Protectant

Uses
for the treatment and/or prevention of diaper rash
temporarily protects and helps relieve chapped or cracked skin

Warnings
For external use only.
When using this product

- do not get into eyes

Do not use on

- deep or puncture wounds
- animal bites
- serious burns

Stop use and ask a doctor if

- condition worsens
- symptoms last more than 7 days or clear up and occur again within a few days

Keep out of reach of children.
If swallowed, get medical help or contact a poison control center right away.

Directions

- Cleanse skin with Thera Moisturizing Body Cleanser or Thera Foaming Body Cleanser
- Apply cream liberally until entire area is covered
- Apply as needed

OTHER SAFETY INFORMATION

Store at 40-95ºF (4-35ºC)

Inactive Ingredients:
Purified Water, Glyceryl Stearate, PEG 100 Stearate, Stearic Acid, Aleurites Moluccana Seed Oil,
Cetyl Alcohol, Glycerin, Butylene Glycol, Carthamus Tinctorius (Safflower) Seed Oil,
Dimethicone Crosspolymer, Calcium Pantothenate (Vitamin B5), Maltodextrin, Niacinamide (Vitamin B3),
Pyridoxine HCL (Vitamin B6), Silica, Sodium Ascorbyl Phosphate (Vitamin C), Sodium Starch Octenylsuccinate,
Tocopheryl Acetate (Vitamin E), Disodium EDTA, Sodium Hyaluronate, Aloe Barbadensis Leaf Extract,
Zingiber Officinale (Ginger) Root Extract, Carthamus Tinctorius (Safflower) Oleosomes, Fragrance,
Phenoxyethanol, Caprylyl Glycol, Chlorphenesin, Bisabolol, Lysine, Histidine, Arginine, Aspartic Acid,
Threonine, Serine, Glutamic Acid, Proline, Glycine, Alanine, Valine, Methionine, Isoleucine, Leucine,
Tyrosine, Phenylalanine, Cysteine, Triethanolamine

Questions?
Call 1-800-777-4908

PACKAGE LABEL

NDC 68599-0213-4
McKesson
Thera
DIMETHICONE BODY SHIELD
Provides mild skin protection against irritation from chapped or cracked skin.
Single Patient Use
NET CONTENTS 4 fl oz (118 mL)
MFR # 53-DS4